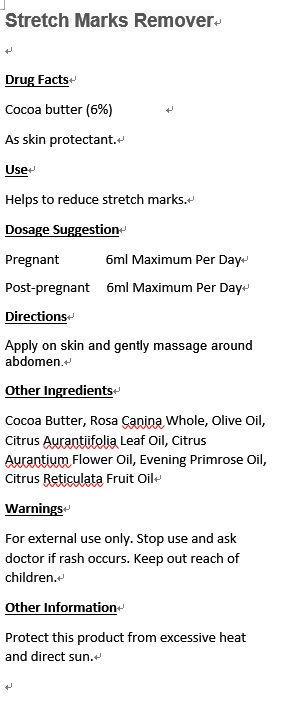 DRUG LABEL: Dermatitica Synergy
NDC: 70470-1008 | Form: OIL
Manufacturer: PHYTOPIA CO., LTD.
Category: otc | Type: HUMAN OTC DRUG LABEL
Date: 20161024

ACTIVE INGREDIENTS: COCOA BUTTER 3.2 mg/50 mL
INACTIVE INGREDIENTS: GERANIUM OIL, ALGERIAN TYPE; SANDALWOOD OIL; EVENING PRIMROSE OIL; ROSA CANINA WHOLE; TANSY OIL; MATRICARIA CHAMOMILLA FLOWERING TOP OIL; OLIVE OIL

Drug Facts

Cocoa butter (6%)

As skin protectant.

Use

Helps to reduce stretch marks.

Dosage Suggestion

Pregnant 6ml Maximum Per Day

Post-pragnant 6ml Maximum Per Day

Directions

Apply on skin and gentlely massage around abdomen.

INACTIVE INGREDIENT

Other Ingredients

Rosa Canina Whole, Olive Oil, Citrus Aurantiifolia Leaf Oil, Citrus Aurantium Flower Oil, Evening Primrose Oil, Citrus Reticulata Fruit Oil

Warnings

For external use only. Stop use and ask doctor if rash occurs. Keep out reach of children.

Other Information

Protect this product from excessive heat and direct sun.

Warnings

For external use only. Stop use and ask doctor if rash occurs. Keep out reach of children.

Stretch Marks Remover